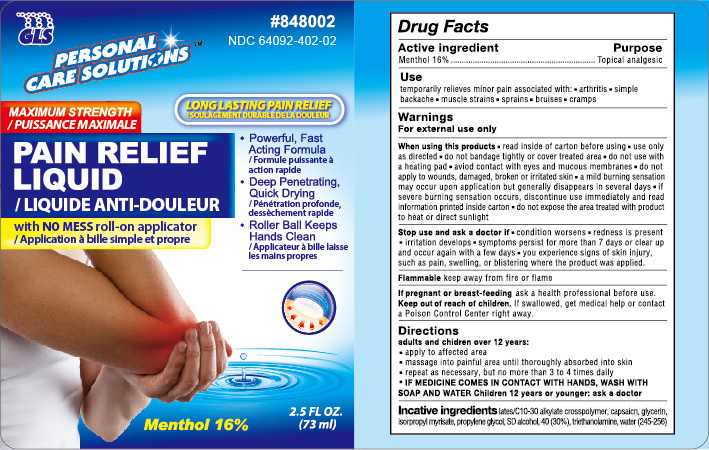 DRUG LABEL: Pain Relief Liquid
NDC: 64092-402 | Form: LIQUID
Manufacturer: Great Lakes Wholesale, Marking, and Sales, Inc.
Category: otc | Type: HUMAN OTC DRUG LABEL
Date: 20161205

ACTIVE INGREDIENTS: MENTHOL 0.16 g/1 mL
INACTIVE INGREDIENTS: GLYCERIN; TROLAMINE; ISOPROPYL MYRISTATE; PROPYLENE GLYCOL; WATER; CAPSAICIN

ACTIVE INGREDIENT

Menthol 16%

PURPOSE

Topical analgesic

INDICATIONS AND USAGE

temporariy relieves minor pain associated with:

- arthritis
- simple backache
- muscle strains
- sprains
- bruises
- cramps

WARNINGS

For external use only

When using this product

- use only as directed
- do not bandage tightly or use with a heating pad
- avoid contact with eyes and mucous membranes
- do not apply to wounds or damaged, broken or irritated skin
- a transient burning sensation may occur upon application but generally disappears in several days
- if severe burning sensation occurs, discontinue use immediately
- do not expose the area treated with product to heat or direct sunlight

Flammable

- keep away from fire or flame

stop use and ask a doctor if

- condition worsens
- redness is present
- irritation develops
- symptoms persist for more than 7 days or clear up and occur again witin a few days sy

PREGNANCY OR BREAST FEEDING

If pregnant or breast-feeding, ask a health professional before use.

KEEP OUT OF REACH OF CHILDREN

If swallowed, get medical help, or contact a Poison control Center right away

INSTRUCTIONS FOR USE

Adults and children over 12 years;

- apply generously to affected area
- massage into painful area until thoroughly absorbed into skin
- repeat as necessary, but no more than 3-4 times daily
- IF MEDICINE COMES IN CONTACT WITH HANDS, WASH WITH SOAP AND WATER

children 12 years or younger: ask a doctor

INACTIVE INGREDIENT

acrylates/C10-30 alkyl acrylate crosspolymer, capsaicin, glycerin, isopropyl myristate, propylene glycol, SD alcohol 40 (3

0%), water (245-256)

DESCRIPTION

Personal Care Solutions

Maximum Strength

Pain Relief Liquid

with no mess roll-on applicator

Long lasting pain relief

- Powerful, fast acting formula
- Deep Penetrating Quick Drying
- Roller Ball Keeps Hands Clean

2.5 fl. oz. (73 ml)

DOSAGE AND ADMINISTRATION

Adults and children over 12 years

- apply generously to affected area
- massage into painful area until thoroughly absorbed int skin
- repeat as necessary, but no more than 3-4 times daily.